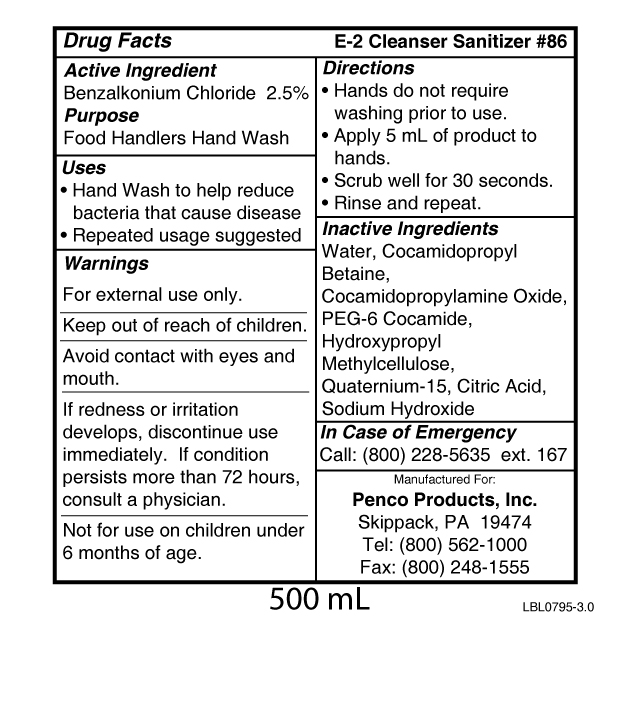 DRUG LABEL: E-2 Cleanser Sanitizer 86
NDC: 42497-086 | Form: SOAP
Manufacturer: Penco Products, Inc.
Category: otc | Type: HUMAN OTC DRUG LABEL
Date: 20100521

ACTIVE INGREDIENTS: Benzalkonium Chloride 2.5 g/100 g
INACTIVE INGREDIENTS: Water; Cocamidopropyl Betaine; Quaternium-15; Citric Acid Monohydrate; Sodium Hydroxide; Hypromellose

Active Ingredient
Benzalkonium Chloride 2.5%

Purpose
Food Handlers Hand Wash

Uses

- Hand wash to help reduce bacteria that cause disease
- Repeated usage suggested

Warnings

For external use only.
Keep out of reach of children.
Avoid contact with eyes and mouth.
If redness develops, discontinue use immediately. If condition persists for
more than 72 hours, consult a physician.
Not for use on children under 6 months of age.

Directions

- Hands do not require washing prior to use.
- Apply 5 mL of product to hands.
- Scrub well for 30 seconds.
- Rinse and repeat.

Inactive Ingredients
Water, Cocamidopropyl Betaine, Cocamidopropylamine Oxide, PEG-6 Cocamide, Hydroxypropyl Methylcellulose, Quaternium-15, Citric Acid, Sodium
Hydroxide

QUESTIONS

In Case of Emergency
Call: (800) 228-5635 ext. 167